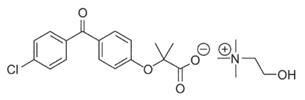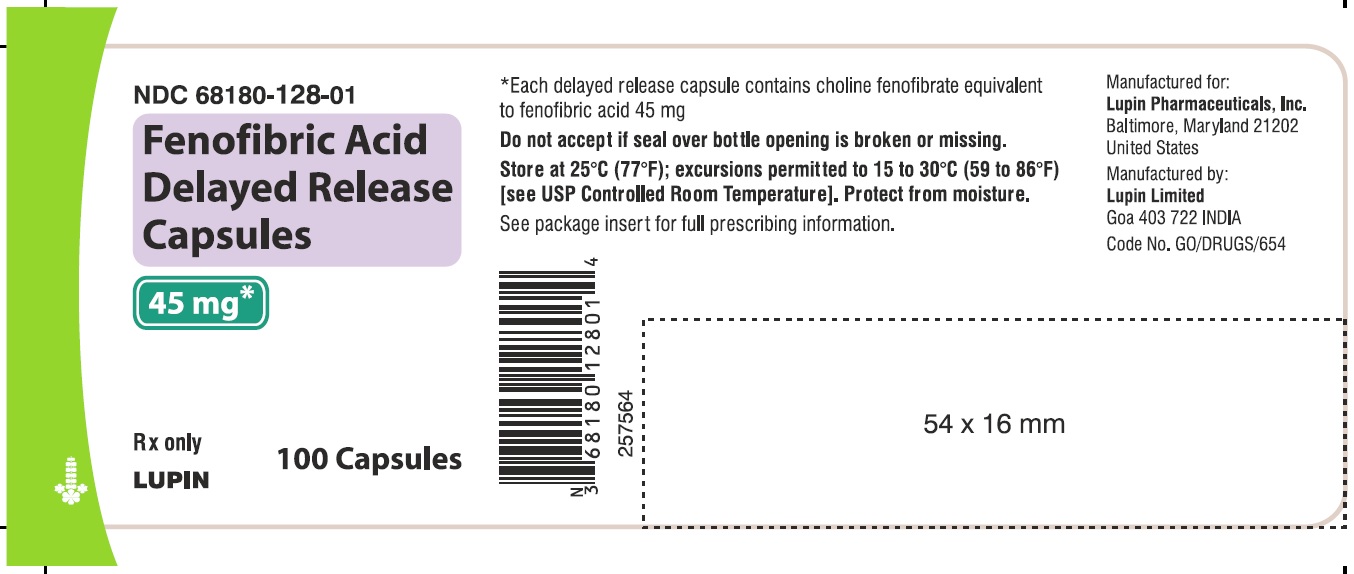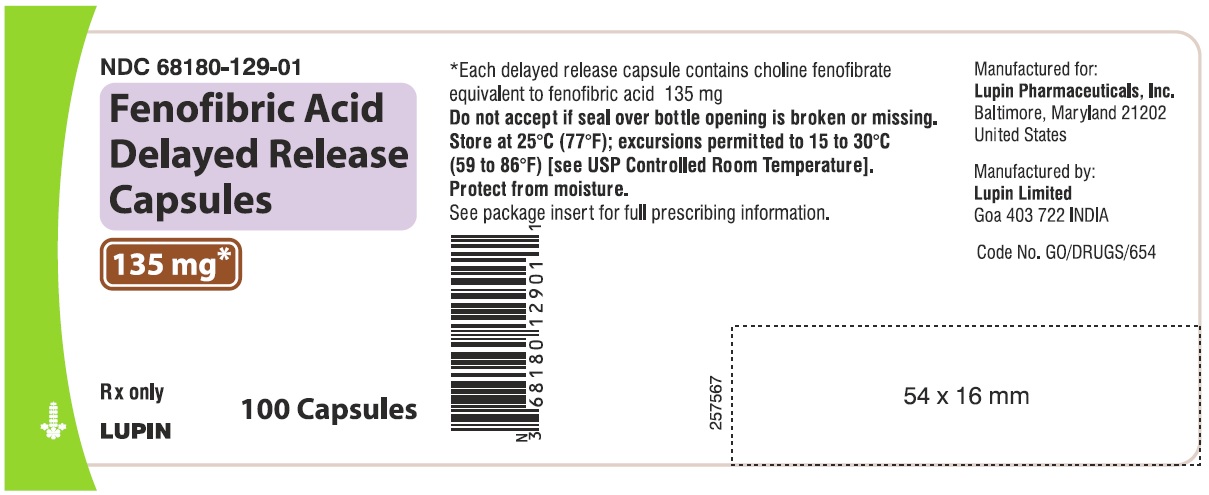 DRUG LABEL: Fenofibric acid
NDC: 68180-128 | Form: CAPSULE, DELAYED RELEASE
Manufacturer: Lupin Pharmaceuticals, Inc.
Category: prescription | Type: HUMAN PRESCRIPTION DRUG LABEL
Date: 20231208

ACTIVE INGREDIENTS: CHOLINE FENOFIBRATE 45 mg/1 1
INACTIVE INGREDIENTS: DIBUTYL SEBACATE; ETHYLCELLULOSES; FERRIC OXIDE RED; FERRIC OXIDE YELLOW; FERROSOFERRIC OXIDE; GELATIN; HYPROMELLOSES; LACTOSE MONOHYDRATE; MAGNESIUM STEARATE; METHACRYLIC ACID AND ETHYL ACRYLATE COPOLYMER; POTASSIUM HYDROXIDE; POVIDONE K90; PROPYLENE GLYCOL; SHELLAC; SILICON DIOXIDE; SODIUM LAURYL SULFATE; SODIUM STEARYL FUMARATE; TALC; TITANIUM DIOXIDE; TRIETHYL CITRATE

HIGHLIGHTS OF PRESCRIBING INFORMATION

These highlights do not include all the information needed to use FENOFIBRIC ACID DELAYED-RELEASE CAPSULES safely and effectively. See full prescribing information for FENOFIBRIC ACID DELAYED-RELEASE CAPSULES.
FENOFIBRIC ACID delayed-release capsules for oral use
Initial U.S. Approval: 2008

RECENT MAJOR CHANGES

Warnings and Precautions, Hepatotoxicity (5.2) 03/2021

1 INDICATIONS AND USAGE

Fenofibric acid delayed-release capsule is a peroxisome proliferator-activated receptor (PPAR) alpha agonist indicated as adjunctive therapy to diet to:

- Reduce TG in patients with severe hypertriglyceridemia (1.1).
- Reduce elevated LDL-C, Total-C, TG and Apo B, and to increase HDLC in patients with primary hypercholesterolemia or mixed dyslipidemia (1.2).

Limitations of Use: Fenofibrate at a dose equivalent to 135 mg of fenofibric acid delayed-release capsule did not reduce coronary heart disease morbidity and mortality in patients with type 2 diabetes mellitus (5.1).

2 DOSAGE AND ADMINISTRATION

- Hypertriglyceridemia: 45 to 135 mg once daily (2.2).
- Primary hypercholesterolemia or mixed dyslipidemia: 135 mg once daily (2.3).
- Renally impaired patients: 45 mg once daily (2.4).
- Maximum dose: 135 mg once daily (2.1).
- May be taken without regard to food (2.1).

3 DOSAGE FORMS AND STRENGTHS

Oral Delayed-Release Capsules: 45 mg and 135 mg (3).

4 CONTRAINDICATIONS

- Severe renal dysfunction, including patients receiving dialysis (4, 12.3).
- Active liver disease (4, 5.2).
- Gallbladder disease (4, 5.5).
- Nursing mothers (4, 8.2).
- Known hypersensitivity to fenofibric acid or fenofibrate (4, 5.9)

5 WARNINGS AND PRECAUTIONS

- Hepatotoxicity: Serious drug-induced liver injury, including liver transplantation and death, has been reported with fenofibric acid. Monitor patient's liver function, including serum ALT, AST, and total bilirubin, at baseline and periodically for the duration of therapy. Discontinue if signs or symptoms of liver injury develop or if elevated enzyme levels persist (5.2).
- Myopathy and rhabdomyolysis: Have been reported in patients taking fenofibrate. Risks are increased in elderly patients and patients with diabetes, renal failure, hypothyroidism, or statin co-administration (5.3).
- Serum creatinine: Fenofibric acid can reversibly increase serum creatinine levels (5.4). Monitor renal function periodically in patients with renal insufficiency (8.6).
- Cholelithiasis: Fenofibric acid increases cholesterol excretion into the bile, leading to risk of cholelithiasis. If suspected, gallbladder studies are indicated (5.5).
- Coumarin anticoagulants: Use caution in concomitant treatment with oral coumarin anticoagulants. Adjust the dosage of coumarin anticoagulant to maintain the prothrombin time/INR at the desired level to prevent bleeding complications (5.6).
- Hypersensitivity reactions: Acute hypersensitivity reactions, including anaphylaxis and angioedema, and delayed hypersensitivity reactions, including severe cutaneous adverse drug reactions have been reported postmarketing. Some cases were life-threatening and required emergency treatment. Discontinue fenofibrate and treat patients appropriately if reactions occur (5.9).

6 ADVERSE REACTIONS

The most common adverse events reported during clinical trials with fenofibrate (≥ 2% and at least 1% greater than placebo) were abnormal liver tests, increased AST, increased ALT, increased CPK, and rhinitis (6.1)

To report SUSPECTED ADVERSE REACTIONS, contact Lupin Pharmaceuticals, Inc. at 1-800-399-2561 or FDA at 1-800-FDA-1088 or www.fda.gov/medwatch

7 DRUG INTERACTIONS

- Coumarin Anticoagulants: (7.1).
- Bile Acid Binding Resins: (7.2).
- Immunosuppressants: (7.3).

8 USE IN SPECIFIC POPULATIONS

- Geriatric Use: Dose selection should be made based on renal function (8.5).
- Renal Impairment: Avoid use in severe renal impairment patients. Dose adjustment is required in mild to moderate renal impairment patients (8.6).

FULL PRESCRIBING INFORMATION

1 INDICATIONS AND USAGE

1.1 Treatment of Severe Hypertriglyceridemia

Fenofibric acid delayed-release capsules are indicated as adjunctive therapy to diet to reduce triglycerides (TG) in patients with severe hypertriglyceridemia. Improving glycemic control in diabetic patients showing fasting chylomicronemia will usually obviate the need for pharmacological intervention. Markedly elevated levels of serum triglycerides (e.g. > 2,000 mg/dL) may increase the risk of developing pancreatitis. The effect of fenofibric acid delayed-release capsules therapy on reducing this risk has not been adequately studied.

1.2 Treatment of Primary Hypercholesterolemia or Mixed Dyslipidemia

Fenofibric acid delayed-release capsules are indicated as adjunctive therapy to diet to reduce elevated low-density lipoprotein cholesterol (LDL-C), total cholesterol (Total-C), triglycerides (TG), and apolipoprotein B (Apo B), and to increase high-density lipoprotein cholesterol (HDL-C) in patients with primary hypercholesterolemia or mixed dyslipidemia.

1.3 Limitations of Use

Fenofibrate at a dose equivalent to 135 mg of fenofibric acid delayed-release capsules did not reduce coronary heart disease morbidity and mortality in 2 large, randomized controlled trials of patients with type 2 diabetes mellitus [see Warnings and Precautions (5.1)].

1.4 General Considerations for Treatment

Laboratory studies should be performed to establish that lipid levels are abnormal before instituting fenofibric acid delayed-release capsules therapy.

Every reasonable attempt should be made to control serum lipids with non-drug methods including appropriate diet, exercise, weight loss in obese patients, and control of any medical problems such as diabetes mellitus and hypothyroidism that may be contributing to the lipid abnormalities. Medications known to exacerbate hypertriglyceridemia (beta-blockers, thiazides, estrogens) should be discontinued or changed if possible, and excessive alcohol intake should be addressed before triglyceride-lowering drug therapy is considered. If the decision is made to use lipid-altering drugs, the patient should be instructed that this does not reduce the importance of adhering to diet.

Drug therapy is not indicated for patients who have elevations of chylomicrons and plasma triglycerides, but who have normal levels of VLDL.

2 DOSAGE AND ADMINISTRATION

2.1 General Considerations

Patients should be placed on an appropriate lipid-lowering diet before receiving fenofibric acid delayed-release capsules, and should continue this diet during treatment. Fenofibric acid delayed-release capsules can be taken without regard to meals. Patients should be advised to swallow fenofibric acid delayed-release capsules whole. Do not open, crush, dissolve, or chew capsules. Serum lipids should be monitored periodically.

2.2 Severe Hypertriglyceridemia

The initial dose of fenofibric acid delayed-release capsules is 45 to 135 mg once daily. Dosage should be individualized according to patient response, and should be adjusted if necessary following repeat lipid determinations at 4 to 8 week intervals. The maximum dose is 135 mg once daily.

2.3 Primary Hypercholesterolemia or Mixed Dyslipidemia

The dose of fenofibric acid delayed-release capsules is 135 mg once daily.

2.4 Impaired Renal Function

Treatment with fenofibric acid delayed-release capsules should be initiated at a dose of 45 mg once daily in patients with mild to moderate renal impairment and should only be increased after evaluation of the effects on renal function and lipid levels at this dose. The use of fenofibric acid delayed-release capsules should be avoided in patients with severely impaired renal function [see Use in Specific Populations (8.6) and Clinical Pharmacology (12.3)].

2.5 Geriatric Patients

Dose selection for the elderly should be made on the basis of renal function [see Use in Specific Populations (8.5)].

3 DOSAGE FORMS AND STRENGTHS

- Fenofibric acid delayed-release capsules, 45 mg have size ‘3’ capsule with brown cap and yellow body, imprinted with "LU" on cap and "Q41" on body in black ink, containing four white to off white mini-tablets.
- Fenofibric acid delayed-release capsules, 135 mg have size ‘0’ capsule with blue opaque cap and yellow opaque body, imprinted with "LU" on cap and "Q42" on body in black ink, containing twelve white to off white mini-tablets.

4 CONTRAINDICATIONS

Fenofibric acid is contraindicated in:

- patients with severe renal impairment, including those receiving dialysis[see Clinical Pharmacology (12.3)].
- patients with active liver disease, including those with primary biliary cirrhosis and unexplained persistent liver function abnormalities [see Warnings and Precautions (5.3)].
- patients with preexisting gallbladder disease [see Warnings and Precautions (5.5)].
- nursing mothers [see Use in Specific Populations (8.2)].
- patients with hypersensitivity to fenofibric acid or fenofibrate[see Warnings and Precautions (5.9)].

5 WARNINGS AND PRECAUTIONS

5.1 Mortality and Coronary Heart Disease Morbidity

The effect of fenofibric acid on coronary heart disease morbidity and mortality and non-cardiovascular mortality has not been established. Because of similarities between fenofibric acid and fenofibrate, clofibrate, and gemfibrozil, the findings in the following large randomized, placebo-controlled clinical studies with these fibrate drugs may also apply to fenofibric acid.

The Action to Control Cardiovascular Risk in Diabetes Lipid (ACCORD Lipid) trial was a randomized placebo-controlled study of 5518 patients with type 2 diabetes mellitus on background statin therapy treated with fenofibrate. The mean duration of follow-up was 4.7 years. Fenofibrate plus statin combination therapy showed a non-significant 8% relative risk reduction in the primary outcome of major adverse cardiovascular events (MACE), a composite of non-fatal myocardial infarction, non-fatal stroke, and cardiovascular disease death (hazard ratio [HR] 0.92, 95% CI 0.79 to 1.08) (p=0.32) as compared to statin monotherapy. In a gender subgroup analysis, the hazard ratio for MACE in men receiving combination therapy versus statin monotherapy was 0.82 (95% CI 0.69 to 0.99), and the hazard ratio for MACE in women receiving combination therapy versus statin monotherapy was 1.38 (95% CI 0.98 to 1.94) (interaction p=0.01). The clinical significance of this subgroup finding is unclear.

The Fenofibrate Intervention and Event Lowering in Diabetes (FIELD) study was a 5-year randomized, placebo-controlled study of 9795 patients with type 2 diabetes mellitus treated with fenofibrate. Fenofibrate demonstrated a non-significant 11 % relative reduction in the primary outcome of coronary heart disease events (hazard ratio [HR] 0.89, 95% CI 0.75 to 1.05, p = 0.16) and a significant 11% reduction in the secondary outcome of total cardiovascular disease events (HR 0.89 [0.80 to 0.99], p = 0.04). There was a non-significant 11 % (HR 1.11 [0.95, 1.29], p = 0.18) and 19% (HR 1.19 [0.90, 1.57], p = 0.22) increase in total and coronary heart disease mortality, respectively, with fenofibrate as compared to placebo.

In the Coronary Drug Project, a large study of post-myocardial infarction patients treated for 5 years with clofibrate, there was no difference in mortality seen between the clofibrate group and the placebo group. There was, however, a difference in the rate of cholelithiasis and cholecystitis requiring surgery between the two groups (3.0% vs. 1.8%).

In a study conducted by the World Health Organization (WHO), 5000 subjects without known coronary artery disease were treated with placebo or clofibrate for 5 years and followed for an additional one year. There was a statistically significant, higher age-adjusted all-cause mortality in the clofibrate group compared with the placebo group (5.70% vs. 3.96%, p = < 0.01). Excess mortality was due to a 33% increase in non-cardiovascular causes, including malignancy, post-cholecystectomy complications, and pancreatitis. This appeared to confirm the higher risk of gallbladder disease seen in clofibrate-treated patients studied in the Coronary Drug Project.

The Helsinki Heart Study was a large (N = 4081) study of middle-aged men without a history of coronary artery disease. Subjects received either placebo or gemfibrozil for 5 years, with a 3.5 year open extension afterward. Total mortality was numerically higher in the gemfibrozil randomization group but did not achieve statistical significance (p = 0.19, 95% confidence interval for relative risk G:P = 0.91 to 1.64). Although cancer deaths trended higher in the gemfibrozil group (p = 0.11), cancers (excluding basal cell carcinoma) were diagnosed with equal frequency in both study groups. Due to the limited size of the study, the relative risk of death from any cause was not shown to be different than that seen in the 9 year follow-up data from WHO study (RR = 1.29). A secondary prevention component of the Helsinki Heart Study enrolled middle-aged men excluded from the primary prevention study because of known or suspected coronary heart disease. Subjects received gemfibrozil or placebo for 5 years. Although cardiac deaths trended higher in the gemfibrozil group, this was not statistically significant (hazard ratio 2.2, 95% confidence interval: 0.94 to 5.05).

5.2 Hepatotoxicity

Serious drug-induced liver injury (DILI), including liver transplantation and death, have been reported postmarketing with fenofibric acid. DILI has been reported within the first few weeks of treatment or after several months of therapy and in some cases has reversed with discontinuation of fenofibric acid delayed-release capsules treatment. Patients with DILI have experienced signs and symptoms including dark urine, abnormal stool, jaundice, malaise, abdominal pain, myalgia, weight loss, pruritus, and nausea. Many patients had concurrent elevations of total bilirubin, serum alanine transaminase (ALT), and aspartate transaminase (AST). DILI has been characterized as hepatocellular, chronic active, and cholestatic hepatitis, and cirrhosis has occurred in association with chronic active hepatitis.

In clinical trials, fenofibric acid delayed-release capsules at a dose of 135 mg daily has been associated with increases in serum AST or ALT. The incidence of increases in transaminases observed with fenofibrate therapy may be dose related [see Adverse Reactions (6.1)].

Fenofibric acid delayed-release capsules is contraindicated in patients with active liver disease, including those with primary biliary cirrhosis and unexplained persistent liver function abnormalities [see Contraindications (4)]. Monitor patient's liver function, including serum ALT, AST, and total bilirubin, at baseline and periodically for the duration of therapy with fenofibric acid. Discontinue fenofibric acid delayed-release capsules if signs or symptoms of liver injury develop or if elevated enzyme levels persist (ALT or AST > 3 times the upper limit of normal, or if accompanied by elevation of bilirubin). Do not restart fenofibric acid delayed-release capsules in these patients if there is no alternative explanation for the liver injury.

5.3 Myopathy and Rhabdomyolysis

Fibrates increase the risk of myositis or myopathy and have been associated with rhabdomyolysis. The risk for serious muscle toxicity appears to be increased in elderly patients and in patients with diabetes, renal failure, or hypothyroidism.

Myopathy should be considered in any patient with diffuse myalgias, muscle tenderness or weakness, and/or marked elevations of CPK levels. Patients should promptly report unexplained muscle pain, tenderness or weakness, particularly if accompanied by malaise or fever. CPK levels should be assessed in patients reporting these symptoms, and fenofibric acid should be discontinued if markedly elevated CPK levels occur or myopathy or myositis is suspected or diagnosed.

Data from observational studies suggest that the risk for rhabdomyolysis is increased when fibrates are co-administered with a statin.

Cases of myopathy, including rhabdomyolysis, have been reported with fenofibrates co-administered with colchicine, and caution should be exercised when prescribing fenofibrate with colchicine [see Drug Interactions (7.4)].

5.4 Serum Creatinine

Reversible elevations in serum creatinine have been reported in patients receiving fenofibric acid as well as patients receiving fenofibrate. In the pooled analysis of three 12-week, double-blind, controlled studies of fenofibric acid, increases in creatinine to > 2 mg/dL occurred in 0.8% of patients treated with fenofibric acid without other lipid-altering drugs. Elevations in serum creatinine were generally stable over time with no evidence for continued increases in serum creatinine with long-term therapy and tended to return to baseline following discontinuation of treatment. The clinical significance of these observations is unknown. Monitoring renal function in patients with renal impairment taking fenofibric acid is suggested. Renal monitoring should be considered for patients at risk for renal insufficiency, such as the elderly and those with diabetes.

5.5 Cholelithiasis

Fenofibric acid, like fenofibrate, clofibrate, and gemfibrozil, may increase cholesterol excretion into the bile, potentially leading to cholelithiasis. If cholelithiasis is suspected, gallbladder studies are indicated. Fenofibric acid therapy should be discontinued if gallstones are found.

5.6 Coumarin Anticoagulants

Caution should be exercised when fenofibric acid is given in conjunction with oral coumarin anticoagulants. Fenofibric acid may potentiate the anticoagulant effects of these agents resulting in prolongation of the prothrombin time/International Normalized Ratio (PT/INR). Frequent monitoring of PT/INR and dose adjustment of the oral anticoagulant are recommended until the PT /INR has stabilized in order to prevent bleeding complications [see Drug Interactions (7.1)].

5.7 Pancreatitis

Pancreatitis has been reported in patients taking drugs of the fibrate class, including fenofibric acid. This occurrence may represent a failure of efficacy in patients with severe hypertriglyceridemia, a direct drug effect, or a secondary phenomenon mediated through biliary tract stone or sludge formation with obstruction of the common bile duct.

5.8 Hematological Changes

Mild to moderate hemoglobin, hematocrit, and white blood cell decreases have been observed in patients following initiation of fenofibric acid and fenofibrate therapy. However, these levels stabilize during long-term administration. Thrombocytopenia and agranulocytosis have been reported in individuals treated with fenofibrates. Periodic monitoring of red and white blood cell counts are recommended during the first 12 months of fenofibric acid administration.

5.9 Hypersensitivity Reactions

Acute Hypersensitivity

Anaphylaxis and angioedema have been reported postmarketing with fenofibrate. In some cases, reactions were life-threatening and required emergency treatment. If a patient develops signs or symptoms of an acute hypersensitivity reaction, advise them to seek immediate medical attention and discontinue fenofibrate.

Delayed Hypersensitivity

Severe cutaneous adverse drug reactions (SCAR), including Stevens-Johnson syndrome, toxic epidermal necrolysis, and Drug Reaction with Eosinophilia and Systemic Symptoms (DRESS), have been reported postmarketing, occurring days to weeks after initiation of fenofibrate. The cases of DRESS were associated with cutaneous reactions (such as rash or exfoliative dermatitis) and a combination of eosinophilia, fever, systemic organ involvement (renal, hepatic, or respiratory). Discontinue fenofibrate and treat patients appropriately if SCAR is suspected.

5.10 Venothromboembolic Disease

In the FIELD trial, pulmonary embolus (PE) and deep vein thrombosis (DVT) were observed at higher rates in the fenofibrate- than the placebo-treated group. Of 9,795 patients enrolled in FIELD, there were 4,900 in the placebo group and 4,895 in the fenofibrate group. For DVT, there were 48 events (1 %) in the placebo group and 67 (1 %) in the fenofibrate group (p = 0.074); and for PE, there were 32 (0.7%) events in the placebo group and 53 (1 %) in the fenofibrate group (p = 0.022).

In the Coronary Drug Project, a higher proportion of the clofibrate group experienced definite or suspected fatal or nonfatal PE or thrombophlebitis than the placebo group (5.2% vs. 3.3% at five years; p < 0.01).

5.11 Paradoxical Decreases in HDL Cholesterol Levels

There have been postmarketing and clinical trial reports of severe decreases in HDL cholesterol levels (as low as 2 mg/dL) occurring in diabetic and non-diabetic patients initiated on fibrate therapy. The decrease in HDL-C is mirrored by a decrease in apolipoprotein A1. This decrease has been reported to occur within 2 weeks to years after initiation of fibrate therapy. The HDL-C levels remain depressed until fibrate therapy has been withdrawn; the response to withdrawal of fibrate therapy is rapid and sustained. The clinical significance of this decrease in HDL-C is unknown. It is recommended that HDL-C levels be checked within the first few months after initiation of fibrate therapy. If a severely depressed HDL-C level is detected, fibrate therapy should be withdrawn, and the HDL-C level monitored until it has returned to baseline, and fibrate therapy should not be re-initiated.

6 ADVERSE REACTIONS

The following serious adverse reactions are described below and elsewhere in the labeling:

- Mortality and coronary heart disease morbidity [see Warnings and Precautions (5.1)]
- Hepatoxicity [see Warnings and Precautions (5.2)]
- Pancreatitis [see Warnings and Precautions (5.7)]
- Hypersensitivity reactions [see Warnings and Precautions (5.9)]
- Venothromboembolic disease [see Warnings and Precautions (5.10)]

6.1 Clinical Trials Experience

Because clinical studies are conducted under widely varying conditions, adverse reaction rates observed in the clinical studies of a drug cannot be directly compared to rates in the clinical studies of another drug and may not reflect the rates observed in practice.

Fenofibric acid is the active metabolite of fenofibrate. Adverse events reported by 2% or more of patients treated with fenofibrate and greater than placebo during double-blind, placebo-controlled trials are listed in Table 1. Adverse events led to discontinuation of treatment in 5.0% of patients treated with fenofibrate and in 3.0% treated with placebo. Increases in liver tests were the most frequent events, causing discontinuation of fenofibrate treatment in 1.6% of patients in double-blind trials.

Table 1. Adverse Events Reported by 2% or More of Patients Treated with Fenofibrate and Greater than Placebo During the Double-Blind, Placebo-Controlled Trials
BODY SYSTEM Adverse Event | Fenofibrate [Dosage equivalent to 135 mg fenofibric acid] (N = 439) | Placebo (N = 365)
BODY AS A WHOLE
Abdominal Pain | 4.6% | 4.4%
Back Pain | 3.4% | 2.5%
Headache | 3.2% | 2.7%
DIGESTIVE
Nausea | 2.3% | 1.9%
Constipation | 2.1% | 1.4%
INVESTIGATIONS
Abnormal Liver Tests | 7.5% | 1.4%
Increased AST | 3.4% | 0.5%
Increased ALT | 3.0% | 1.6%
Increased Creatine Phosphokinase | 3.0% | 1.4%
RESPIRATORY
Respiratory Disorder | 6.2% | 5.5%
Rhinitis | 2.3% | 1.1%

Urticaria was seen in 1.1% vs. 0%, and rash in 1.4% vs. 0.8% of fenofibrate and placebo patients respectively in controlled trials.

Clinical trials with fenofibric acid did not include a placebo-control arm. However, the adverse event profile of fenofibric acid was generally consistent with that of fenofibrate. The following adverse events not listed above were reported in ≥ 3% of patients taking fenofibric acid alone:

Gastrointestinal Disorders:

Diarrhea, dyspepsia

General Disorders and Administration Site Conditions:

Pain

Infections and Infestations:

Nasopharyngitis, sinusitis, upper respiratory tract infection

Musculoskeletal and Connective Tissue Disorders:

Arthralgia, myalgia, pain in extremity

Nervous System Disorders:

Dizziness

Increases in Liver Enzymes

In a pooled analysis of three 12-week, double-blind, controlled studies of fenofibric acid, increases in ALT and AST> 3 times the upper limit of normal on two consecutive occasions occurred in 1.9% and 0.2%, respectively, of patients receiving fenofibric acid delayed-release capsules 135 mg daily and placebo, without other lipid-altering drugs. In a pooled analysis of 10 placebo-controlled trials, increases to > 3 times the upper limit of normal in ALT occurred in 5.3% of patients taking fenofibrate versus 1.1% of patients treated with placebo. In an 8-week study, the incidence of ALT or AST elevations ≥ 3 times the upper limit of normal was 13% in patients receiving dosages equivalent to 90 mg to 135 mg fenofibric acid daily and was 0% in those receiving dosages equivalent to 45 mg or less fenofibric acid delayed-release capsules daily or placebo.

6.2 Postmarketing Experience

The following adverse reactions have been identified during postapproval use of fenofibrate. Because these reactions are reported voluntarily from a population of uncertain size, it is not always possible to reliably estimate their frequency or establish a causal relationship to drug exposure: rhabdomyolysis, pancreatitis, renal failure, muscle spasms, acute renal failure, hepatitis, cirrhosis, increased total bilirubin, anemia, asthenia, severely depressed HDL-cholesterol levels, and interstitial lung disease. Photosensitivity reactions to fenofibrate have occurred days to months after initiation; in some of these cases, patients reported a prior photosensitivity reaction to ketoprofen.

7 DRUG INTERACTIONS

7.1 Coumarin Anticoagulants

Potentiation of coumarin-type anticoagulant effect has been observed with prolongation of the PT/INR.

Caution should be exercised when oral coumarin anticoagulants are given in conjunction with fenofibric acid. The dosage of the anticoagulant should be reduced to maintain the PT/INR at the desired level to prevent bleeding complications. Frequent PT/INR determinations are advisable until it has been definitely determined that the PT/INR has stabilized [see Warnings and Precautions (5.6)].

7.2 Bile Acid Binding Resins

Since bile acid binding resins may bind other drugs given concurrently, patients should take fenofibric acid at least 1 hour before or 4 to 6 hours after a bile acid resin to avoid impeding its absorption.

7.3 Immunosuppressants

Immunosuppressants such as cyclosporine and tacrolimus can produce nephrotoxicity with decreases in creatinine clearance and rises in serum creatinine, and because renal excretion is the primary elimination route of drugs of the fibrate class including fenofibric acid, there is a risk that an interaction will lead to deterioration of renal function. The benefits and risks of using fenofibric acid with immunosuppressants and other potentially nephrotoxic agents should be carefully considered, and the lowest effective dose employed.

7.4 Colchicine

Cases of myopathy, including rhabdomyolysis, have been reported with fenofibrates co-administered with colchicine, and caution should be exercised when prescribing fenofibrate with colchicine.

8 USE IN SPECIFIC POPULATIONS

8.1 Pregnancy

Risk Summary

Limited available data with fenofibrate use in pregnant women are insufficient to determine a drug associated risk of major birth defects, miscarriage or adverse maternal or fetal outcomes. In animal reproduction studies, no evidence of embryo-fetal toxicity was observed with oral administration of fenofibrate in rats and rabbits during organogenesis at doses less than or equivalent to the maximum recommended clinical dose of 135 mg daily, based on body surface area (mg/m^2). Adverse reproductive outcomes occurred at higher doses in the presence of maternal toxicity (see Data). Fenofibric acid should be used during pregnancy only if the potential benefit justifies the potential risk to the fetus.

The estimated background risk of major birth defects and miscarriage for the indicated population is unknown. In the U.S. general population, the estimated background risk of major birth defects and miscarriage in clinically recognized pregnancies is 2 to 4% and 15 to 20%, respectively.

Data

Animal Data:

In pregnant rats given oral dietary doses of 14, 127, and 361 mg/kg/day from gestation day 6 to 15 during the period of organogenesis, no adverse developmental findings were observed at 14 mg/kg/day (less than the clinical exposure at the maximum recommended human dose [MRHD] of 300 mg fenofibrate daily, equivalent to 135 mg fenofibric acid daily, based on body surface area comparisons). Increased fetal skeletal malformations were observed at maternally toxic doses (361 mg/kg/day, corresponding to 12 times the clinical exposure at the MRHD) that significantly suppressed maternal body weight gain.

In pregnant rabbits given oral gavage doses of 15, 150, and 300 mg/kg/day from gestation day 6 to 18 during the period of organogenesis and allowed to deliver, no adverse developmental findings were observed at 15 mg/kg/day (a dose that approximates the clinical exposure at the MRHD, based on body surface area comparisons). Aborted litters were observed at maternally toxic doses (≥ 150 mg/kg/day, corresponding to ≥ 10 times the clinical exposure at the MRHD) that suppressed maternal body weight gain.

In pregnant rats given oral dietary doses of 15, 75, and 300 mg/kg/day from gestation day 15 through lactation day 21 (weaning), no adverse developmental effects were observed at 15 mg/kg/day (less than the clinical exposure at the MRHD, based on body surface area comparisons), despite maternal toxicity (decreased weight gain). Post-implantation loss was observed at ≥ 75 mg/kg/day (≥ 2 times the clinical exposure at the MRHD) in the presence of maternal toxicity (decreased weight gain). Decreased pup survival was noted at 300 mg/kg/day (10 times the clinical exposure at the MRHD), which was associated with decreased maternal body weight gain/maternal neglect.

8.2 Lactation

Risk Summary

There is no available information on the presence of fenofibrate in human milk, effects of the drug on the breastfed infant, or the effects on milk production. Fenofibrate is present in the milk of rats, and is therefore likely to be present in human milk. Because of the potential for serious adverse reactions in breastfed infants, such as disruption of infant lipid metabolism, women should not breastfeed during treatment with fenofibric acid and for 5 days after the final dose [see Contraindications (4)].

8.4 Pediatric Use

The safety and effectiveness of fenofibric acid in pediatric patients have not been established.

8.5 Geriatric Use

Fenofibric acid is substantially excreted by the kidney as fenofibric acid and fenofibric acid glucuronide, and the risk of adverse reactions to this drug may be greater in patients with impaired renal function. Fenofibric acid exposure is not influenced by age. Since elderly patients have a higher incidence of renal impairment, dose selection for the elderly should be made on the basis of renal function [see Dosage and Administration (2.5) and Clinical Pharmacology (12.3)]. Elderly patients with normal renal function should require no dose modifications. Consider monitoring renal function in elderly patients taking fenofibric acid.

8.6 Renal Impairment

The use of fenofibric acid should be avoided in patients who have severe renal impairment [see Contraindications (4)]. Dose reduction is required in patients with mild to moderate renal impairment [see Dosage and Administration (2.4) and Clinical Pharmacology (12.3)]. Monitoring renal function in patients with renal impairment is recommended.

8.7 Hepatic Impairment

The use of fenofibric acid has not been evaluated in subjects with hepatic impairment [see Contraindications (4) and Clinical Pharmacology (12.3)].

10 OVERDOSAGE

There is no specific treatment for overdose with fenofibric acid. General supportive care of the patient is indicated, including monitoring of vital signs and observation of clinical status, should an overdose occur. If indicated, elimination of unabsorbed drug should be achieved by emesis or gastric lavage; usual precautions should be observed to maintain the airway. Because fenofibric acid is highly bound to plasma proteins, hemodialysis should not be considered.

11 DESCRIPTION

Fenofibric acid is a lipid regulating agent available as delayed release capsules for oral administration. Each delayed-release capsule contains choline fenofibrate, equivalent to 45 mg or 135 mg of fenofibric acid. The chemical name for choline fenofibrate is ethanaminium, 2-hydroxy-N,N,N-trimethyl, 2-{4-(4-chlorobenzoyl)phenoxy] -2-methylpropanoate (1:1) with the following structural formula:

Choline Fenofibrate

The empirical formula is C22H28ClNO5 and the molecular weight is 421.91. Choline fenofibrate is freely soluble in water. The melting point is approximately 210°C. Choline fenofibrate is a white to yellow powder, which is stable under ordinary conditions.

Each delayed-release capsule contains enteric coated mini-tablets comprised of choline fenofibrate and the following inactive ingredients: colloidal silicon dioxide, dibutyl sebacate, ethyl cellulose, hypromellose, lactose monohydrate, magnesium stearate, methacrylic acid co polymer, povidone, sodium stearyl fumarate, talc and triethyl citrate. The capsule shell of the 45 mg capsule contains the following inactive ingredients: gelatin, iron oxide black, iron oxide red, iron oxide yellow, sodium lauryl sulphate and titanium dioxide. The capsule shell of the 135 mg capsule contains the following inactive ingredients: FD and C Blue #1, gelatin, iron oxide yellow, sodium lauryl sulphate and titanium dioxide. The capsules are printed with edible ink containing iron oxide black, potassium hydroxide, propylene glycol and shellac.

12 CLINICAL PHARMACOLOGY

12.1 Mechanism of Action

The active moiety of fenofibric acid delayed-release capsule is fenofibric acid. The pharmacological effects of fenofibric acid in both animals and humans have been extensively studied through oral administration of fenofibrate.

The lipid-modifying effects of fenofibric acid seen in clinical practice have been explained in vivo in transgenic mice and in vitro in human hepatocyte cultures by the activation of peroxisome proliferator activated receptor α (PPARα). Through this mechanism, fenofibric acid increases lipolysis and elimination of triglyceride-rich particles from plasma by activating lipoprotein lipase and reducing production of Apo CIII (an inhibitor of lipoprotein lipase activity).

Activation of PPARα also induces an increase in the synthesis of HDL-C and Apo AI and AII.

12.3 Pharmacokinetics

Fenofibric acid delayed-release capsule contains fenofibric acid, which is the only circulating pharmacologically active moiety in plasma after oral administration of fenofibric acid delayed-release capsules. Fenofibric acid is also the circulating pharmacologically active moiety in plasma after oral administration of fenofibrate, the ester of fenofibric acid.

Plasma concentrations of fenofibric acid after administration of one 135 mg fenofibric acid delayed-release capsule are equivalent to those after one 200 mg capsule of micronized fenofibrate administered under fed conditions.

Absorption

Fenofibric acid is well absorbed throughout the gastrointestinal tract. The absolute bioavailability of fenofibric acid is approximately 81%.

Peak plasma levels of fenofibric acid occur within 4 to 5 hours after a single dose administration of fenofibric acid delayed-release capsule under fasting conditions.

Fenofibric acid exposure in plasma, as measured by Cmax and AUC, is not significantly different when a single 135 mg dose of fenofibric acid delayed-release capsule is administered under fasting or nonfasting conditions.

Distribution

Upon multiple dosing of fenofibric acid delayed-release capsules, fenofibric acid levels reach steady state within 8 days. Plasma concentrations of fenofibric acid at steady state are approximately slightly more than double those following a single dose. Serum protein binding is approximately 99% in normal and dyslipidemic subjects.

Metabolism

Fenofibric acid is primarily conjugated with glucuronic acid and then excreted in urine. A small amount of fenofibric acid is reduced at the carbonyl moiety to a benzhydrol metabolite which is, in turn, conjugated with glucuronic acid and excreted in urine.

In vivo metabolism data after fenofibrate administration indicate that fenofibric acid does not undergo oxidative metabolism (e.g., cytochrome P450) to a significant extent.

Elimination

After absorption, fenofibric acid is primarily excreted in the urine in the form of fenofibric acid and fenofibric acid glucuronide.

Fenofibric acid is eliminated with a half-life of approximately 20 hours, allowing once daily administration of fenofibric acid delayed-release capsules.

Specific Populations

Geriatrics :

In five elderly volunteers 77 to 87 years of age, the oral clearance of fenofibric acid following a single oral dose of fenofibrate was 1.2 L/h, which compares to 1.1 L/h in young adults. This indicates that an equivalent dose of fenofibric acid delayed-release capsules can be used in elderly subjects with normal renal function, without increasing accumulation of the drug or metabolites [see Use in Specific Populations (8.5)].

Pediatrics:

The pharmacokinetics of fenofibric acid has not been studied in pediatric populations.

Gender:

No pharmacokinetic difference between males and females has been observed for fenofibric acid delayed-release capsules.

Race:

The influence of race on the pharmacokinetics of fenofibric acid delayed-release capsules has not been studied; however, fenofibric acid is not metabolized by enzymes known for exhibiting inter-ethnic variability.

Renal Impairment:

The pharmacokinetics of fenofibric acid was examined in patients with mild, moderate, and severe renal impairment. Patients with severe renal impairment (estimated glomerular filtration rate [eGFR] <30 mL/min/1.73m^2) showed a 2.7-fold increase in exposure for fenofibric acid and increased accumulation of fenofibric acid during chronic dosing compared to that of healthy subjects. Patients with mild to moderate renal impairment (eGFR 30 to 59 mL/min/1.73m^2) had similar exposure but an increase in the half-life for fenofibric acid compared to that of healthy subjects. Based on these findings, the use of fenofibric acid delayed-release capsules should be avoided in patients who have severe renal impairment and dose reduction is required in patients having mild to moderate renal impairment [see Dosage and Administration (2.4)].

Hepatic Impairment:

No pharmacokinetic studies have been conducted in patients with hepatic impairment.

Drug-drug Interactions

In vitro studies using human liver microsomes indicate that fenofibric acid is not an inhibitor of cytochrome (CYP) P450 isoforms CYP3A4, CYP2D6, CYP2E1, or CYP1A2. It is a weak inhibitor of CYP2C8, CYP2C19, and CYP2A6, and mild-to-moderate inhibitor of CYP2C9 at therapeutic concentrations.

Comparison of atorvastatin exposures when atorvastatin (80 mg once daily for 10 days) is given in combination with fenofibric acid (Fenofibric acid delayed-release capsules 135 mg once daily for 10 days) and ezetimibe (10 mg once daily for 10 days) versus when atorvastatin is given in combination with ezetimibe only (ezetimibe 10 mg once daily and atorvastatin, 80 mg once daily for 10 days): The Cmax decreased by 1 % for atorvastatin and ortho-hydroxy- atorvastatin and increased by 2% for parahydroxy-atorvastatin. The AUC decreased 6% and 9% for atorvastatin and orthohydroxy-atorvastatin, respectively, and did not change for para-hydroxy-atorvastatin.

Comparison of ezetimibe exposures when ezetimibe (10 mg once daily for 10 days) is given in combination with fenofibric acid (Fenofibric acid delayed-release capsules 135 mg once daily for 10 days) and atorvastatin (80 mg once daily for 10 days) versus when ezetimibe is given in combination with atorvastatin only (ezetimibe 10 mg once daily and atorvastatin, 80 mg once daily for 10 days): The Cmax increased by 26% and 7% for total and free ezetimibe, respectively. The AUC increased by 27% and 12% for total and free ezetimibe, respectively.

Table 2 describes the effects of co-administered drugs on fenofibric acid systemic exposure. Table 3 describes the effects of co-administered fenofibric acid on other drugs.

Table 2. Effects of Co-Administered Drugs on Fenofibric Acid Systemic Exposure from Fenofibric Acid Delayed-Release Capsules or Fenofibrate Administration
Co-Administered Drug | Dosage Regimen of Co-Administered Drug | Dosage Regimen of Fenofibric Acid Delayed-Release Capsules or Fenofibrate | Changes in Fenofibric Acid Exposure
 |  |  | AUC | Cmax
Lipid-lowering agents
Rosuvastatin | 40 mg once daily for 10 days | Fenofibric acid delayed-release capsules 135 mg once daily for 10 days | ↓2% | ↓2%
Atorvastatin | 20 mg once daily for 10 days | Fenofibrate 160 mg [TriCor (fenofibrate) oral tablet] once daily for 10 days | ↓2% | ↓4%
Atorvastatin + ezetimibe | Atorvastatin, 80 mg once daily and ezetimibe, 10 mg once daily for 10 days | Fenofibric acid delayed-release capsules 135 mg once daily for 10 days | ↑5% | ↑5%
Pravastatin | 40 mg as a single dose | Fenofibrate 3 x 67 mg [TriCor (fenofibrate) oral micronized capsule] as a single dose | ↓1% | ↓2%
Fluvastatin | 40 mg as a single dose | Fenofibrate 160 mg as a single dose | ↓2% | ↓10%
Simvastatin | 80 mg once daily for 7 days | Fenofibrate 160 mg once daily for 7 days | ↓5% | ↓11%
Anti-diabetic agents
Glimepiride | 1 mg as a single dose | Fenofibrate 145 mg once daily for 10 days | ↑1% | ↓1%
Metformin | 850 mg 3 times daily for 10 days | Fenofibrate 54 mg 3 times daily for 10 days | ↓9% | ↓6%
Rosiglitazone | 8 mg once daily for 5 days | Fenofibrate 145 mg once daily for 14 days | ↑10% | ↑3%
Gastrointestinal agents
Omeprazole | 40 mg once daily for 5 days | Fenofibric acid delayed-release capsules 135 mg as a single dose fasting | ↑6% | ↑17%
Omeprazole | 40 mg once daily for 5 days | Fenofibric acid delayed-release capsules 135 mg as a single dose with food | ↑4% | ↓2%

Table 3. Effects of Fenofibric Acid Delayed-Release Capsules or Fenofibrate Co-Administration on Systemic Exposure of Other Drugs
Dosage Regimen of Fenofibric Acid Delayed-Release Capsules or Fenofibrate | Dosage Regimen of Co-Administered Drug | Change in Co-Administered Drug Exposure
 |  | Analyte | AUC | Cmax
Lipid-lowering agents
Fenofibric acid delayed-release capsules 135 mg once daily for 10 days | Rosuvastatin, 40 mg once daily for 10 days | Rosuvastatin | ↑6% | ↑20%
Fenofibrate 160 mg [TriCor (fenofibrate) oral tablet] once daily for 10 days | Atorvastatin, 20 mg once daily for 10 days | Atorvastatin | ↓17% | 0%
Fenofibrate 3 x 67 mg [TriCor (fenofibrate) oral micronized capsule] as a single dose | Pravastatin, 40 mg as a single dose | Pravastatin | ↑13% | ↑13%
 |  | 3α-Hydroxyl-isopravastatin | ↑26% | ↑29%
Fenofibrate 160 mg as a single dose | Fluvastatin, 40 mg as a single dose | (+)-3R, 5S-Fluvastatin | ↑15% | ↑16%
Fenofibrate 160 mg once daily for 7 days | Simvastatin, 80 mg once daily for 7 days | Simvastatin acid | ↓36% | ↓11%
 |  | Simvastatin | ↓11% | ↓17%
 |  | Active HMG-CoA Inhibitors | ↓12% | ↓1%
 |  | Total HMG-CoA Inhibitors | ↓8% | ↓10%
Anti-diabetic agents
Fenofibrate 145 mg once daily for 10 days | Glimepiride, 1 mg as a single dose | Glimepiride | ↑35% | ↑18%
Fenofibrate 54 mg 3 times daily for 10 days | Metformin, 850 mg 3 times daily for 10 days | Metformin | ↑3% | ↑6%
Fenofibrate 145 mg once daily for 14 days | Rosiglitazone, 8 mg once daily for 5 days | Rosiglitazone | ↑6% | ↓1%

13 NONCLINICAL TOXICOLOGY

13.1 Carcinogenesis, Mutagenesis, Impairment of Fertility

Fenofibric Acid

No carcinogenicity and fertility studies have been conducted with choline fenofibrate or fenofibric acid. However, because fenofibrate is rapidly converted to its active metabolite, fenofibric acid, either during or immediately following absorption both in animals and humans, studies conducted with fenofibrate are relevant for the assessment of the toxicity profile of fenofibric acid. A similar toxicity spectrum is expected after treatment with either fenofibric acid delayed-release capsules or fenofibrate.

Fenofibrate

Two dietary carcinogenicity studies have been conducted in rats with fenofibrate. In the first 24-month study, Wistar rats were dosed with fenofibrate at 10, 45, and 200 mg/kg/day, approximately 0.3, 1, and 6 times the maximum recommended human dose (MRHD) of 300 mg fenofibrate daily, equivalent to 135 mg fenofibric acid delayed-release capsules daily, based on body surface area comparisons. At a dose of 200 mg/kg/day (at 6 times the MRHD), the incidence of liver carcinomas was significantly increased in both sexes. A statistically significant increase in pancreatic carcinomas was observed in males at 1 and 6 times the MRHD; an increase in pancreatic adenomas and benign testicular interstitial cell tumors was observed at 6 times the MRHD in males. In a second 24-month rat carcinogenicity study in a different strain of rats (Sprague-Dawley), doses of 10 and 60 mg/kg/day (0.3 and 2 times the MRHD) produced significant increases in the incidence of pancreatic acinar adenomas in both sexes and increases in testicular interstitial cell tumors in males at 2 times the MRHD.

A 117-week carcinogenicity study was conducted in rats comparing three drugs: fenofibrate 10 and 60 mg/kg/day (0.3 and 2 times the MRHD, based on body surface area comparisons), clofibrate (400 mg/kg/day; 2 times the human dose), and gemfibrozil (250 mg/kg/day; 2 times the human dose, based on mg/m^2 surface area). Fenofibrate increased pancreatic acinar adenomas in both sexes. Clofibrate increased hepatocellular carcinoma and pancreatic acinar adenomas in males and hepatic neoplastic nodules in females. Gemfibrozil increased hepatic neoplastic nodules in males and females, while all three drugs increased testicular interstitial cell tumors in males.

In a 21-month study in CF-l mice, fenofibrate 10, 45, and 200 mg/kg/day (approximately 0.2, 1, and 3 times the MRHD on the basis of mg/m^2 surface area) significantly increased the liver carcinomas in both sexes at 3 times the MRHD. In a second 18-month study at 10, 60, and 200 mg/kg/day, fenofibrate significantly increased the liver carcinomas male mice and liver adenomas in female mice at 3 times the MRHD.

Electron microscopy studies have demonstrated peroxisomal proliferation following fenofibrate administration to the rat. An adequate study to test for peroxisome proliferation in humans has not been done, but changes in peroxisome morphology and numbers have been observed in humans after treatment with other members of the fibrate class when liver biopsies were compared before and after treatment in the same individual.

Fenofibrate has been demonstrated to be devoid of mutagenic potential in the following tests: Ames, mouse lymphoma, chromosomal aberration and unscheduled DNA synthesis in primary rat hepatocytes.

In fertility studies rats were given oral dietary doses of fenofibrate, males received 61 days prior to mating and females 15 days prior to mating through weaning, which resulted in no adverse effect on fertility at doses up to 300 mg/kg/day (10 times the MRHD, based on body surface area comparisons).

14 CLINICAL STUDIES

14.1 Severe Hypertriglyceridemia

The effects of fenofibrate on serum triglycerides were studied in two randomized, double-blind, placebo- controlled clinical trials of 147 hypertriglyceridemic patients. Patients were treated for eight weeks under protocols that differed only in that one entered patients with baseline TG levels of 500 to 1500 mg/dL, and the other TG levels of 350 to 500 mg/dL. In patients with hypertriglyceridemia and normal cholesterolemia with or without hyperchylomicronemia, treatment with fenofibrate at dosages equivalent to 135 mg once daily of fenofibric acid delayed-release capsules decreased primarily VLDL-TG and VLDL-C. Treatment of patients with elevated TG often results in an increase of LDL-C (Table 4).

Table 4. Effects of Fenofibrate in Patients With Severe Hypertriglyceridemia
S tudy 1 | Placebo |  |  |  | Fenofibrate
Baseline TG levels 350 to 499 mg/dL | N | Baseline Mean (mg/dL) | Endpoint Mean (mg/dL) | Mean % Change | N | Baseline Mean (mg/dL) | Endpoint Mean (mg/dL) | Mean % Change
Triglycerides | 28 | 449 | 450 | -0.5 | 27 | 432 | 223 | -46.2 [= p < 0.05 vs. Placebo]
VLDL Triglycerides | 19 | 367 | 350 | 2.7 | 19 | 350 | 178 | -44.1
Total Cholesterol | 28 | 255 | 261 | 2.8 | 27 | 252 | 227 | -9.1
HDL Cholesterol | 28 | 35 | 36 | 4 | 27 | 34 | 40 | 19.6
LDL Cholesterol | 28 | 120 | 129 | 12 | 27 | 128 | 137 | 14.5
VLDL Cholesterol | 27 | 99 | 99 | 5.8 | 27 | 92 | 46 | -44.7
Study 2 | Placebo |  |  |  | Fenofibrate
Baseline TG levels 500 to 1500 mg/dL | N | Baseline Mean (mg/dL) | Endpoint Mean (mg/dL) | Mean % Change | N | Baseline Mean (mg/dL) | Endpoint Mean (mg/dL) |  | Mean % Change
Triglycerides | 44 | 710 | 750 | 7.2 | 48 | 726 | 308 |  | -54.5
VLDL Triglycerides | 29 | 537 | 571 | 18.7 | 33 | 543 | 205 |  | -50.6
Total Cholesterol | 44 | 272 | 271 | 0.4 | 48 | 261 | 223 |  | -13.8
HDL Cholesterol | 44 | 27 | 28 | 5.0 | 48 | 30 | 36 |  | 22.9
LDL Cholesterol | 42 | 100 | 90 | -4.2 | 45 | 103 | 131 |  | 45.0
VLDL Cholesterol | 42 | 137 | 142 | 11.0 | 45 | 126 | 54 |  | -49.4

14.2 Primary Hypercholesterolemia (Heterozygous Familial and Nonfamilial) and Mixed Dyslipidemia

The effects of fenofibrate at a dose equivalent to fenofibric acid delayed-release capsules 135 mg once daily were assessed from four randomized, placebo-controlled, double-blind, parallel-group studies including patients with the following mean baseline lipid values: Total-C 306.9 mg/dL; LDL-C 213.8 mg/dL; HDL-C 52.3 mg/dL; and triglycerides 191.0 mg/dL. Fenofibrate therapy lowered LDL-C, Total-C, and the LDL-C/HDL-C ratio. Fenofibrate therapy also lowered triglycerides and raised HDL-C (Table 5).

Table 5. Mean Percent Change in Lipid Parameters at End of Treatment^1
Treatment Group | Total-C (mg/dL) | LDL-C (mg/dL) | HDL-C (mg/dL) | TG (mg/dL)
Pooled Cohort
Mean baseline lipid values (n = 646) | 306.9 | 213.8 | 52.3 | 191.0
All Fenofibrate (n = 361) | -18.7% [p = < 0.05 vs. Placebo] | -20.6% | +11.0% | -28.9%
Placebo (n = 285) | -0.4% | -2.2% | +0.7% | +7.7%
Baseline LDL-C > 160 mg/dL and TG < 150 mg/dL
Mean baseline lipid values (n = 334) | 307.7 | 227.7 | 58.1 | 101.7
All Fenofibrate (n = 193) | -22.4% | -31.4% | +9.8% | -23.5%
Placebo (n = 141) | +0.2% | -2.2% | +2.6% | +11.7%
Baseline LDL-C > 160 mg/dL and TG ≥ 150 mg/dL
Mean baseline lipid values (n = 242) | 312.8 | 219.8 | 46.7 | 231.9
All Fenofibrate (n = 126) | -16.8% | -20.1% | +14.6% | -35.9%
Placebo (n = 116) | -3.0% | -6.6% | +2.3% | +0.9%
^1Duration of study treatment was 3 to 6 months

In a subset of the subjects, measurements of Apo B were conducted. Fenofibrate treatment significantly reduced Apo B from baseline to endpoint as compared with placebo (-25.1% vs. 2.4%, p < 0.0001, n = 213 and 143, respectively).

16 HOW SUPPLIED/STORAGE AND HANDLING

Fenofibric acid delayed-release capsules are supplied in two dose strengths as follows:

- Fenofibric acid delayed-release capsules, 45 mg are size '3' capsule with brown cap and yellow body, imprinted with "LU" on cap and "Q41" on body in black ink, containing four white to off white mini-tablets. The delayed-release capsules are available in bottles of 90's (NDC 68180-128-09); 100's (NDC 68180-128-01) and 500's (NDC 68180-128-02).
- Fenofibric acid delayed-release capsules, 135 mg are size '0' capsule with blue opaque cap and yellow opaque body, imprinted with "LU" on cap and "Q42" on body in black ink, containing twelve white to off white mini-tablets. The delayed-release capsules are available in bottle of 90's (NDC 68180-129-09); 100's (NDC 68180-129-01) and 500's (NDC 68180-129-02).

Store at 25°C (77°F); excursions permitted to 15 to 30°C (59 to 86°F). [see USP Controlled Room Temperature]. Keep out of the reach of children. Protect from moisture.

17 PATIENT COUNSELING INFORMATION

Patients should be advised:

- of the potential benefits and risks of fenofibric acid delayed-release capsules.
- not to use fenofibric acid delayed-release capsules if there is a known hypersensitivity to fenofibrate or fenofibric acid.
- of medications that should not be taken in combination with fenofibric acid delayed-release capsules.
- that if they are taking coumarin anticoagulants, fenofibric acid delayed-release capsules may increase their anti-coagulant effect, and increased monitoring may be necessary.
- to continue to follow an appropriate lipid-modifying diet while taking fenofibric acid delayed-release capsules.
- to take fenofibric acid delayed-release capsules once daily, without regard to food, at the prescribed dose, swallowing each capsule whole.
- to return to their physician's office for routine monitoring.
- to inform their physician of all medications, supplements, and herbal preparations they are taking and any change to their medical condition. Patients should also be advised to inform their physicians prescribing a new medication that they are taking fenofibric acid delayed-release capsules.
- to inform their physician of symptoms of liver injury (e.g., jaundice, abdominal pain, nausea, malaise, dark urine, abnormal stool, pruritus); any muscle pain, tenderness, or weakness; or any other new symptoms.
- not to breastfeed during treatment with fenofibric acid delayed-release capsules and for 5 days after the final dose.

* The brands listed are trademarks of their respective owners and are not trademarks of Lupin Pharmaceuticals, Inc. The makers of these brands are not affiliated with and do not endorse Lupin Pharmaceuticals, Inc. or its products.

Manufactured for

Lupin Pharmaceuticals, Inc.

Baltimore, Maryland 21202

United States

Manufactured by:

Lupin Limited

Goa - 403 722

INDIA

Revised: July 2021 ID#: 268317

PACKAGE LABEL PRINCIPAL DISPLAY PANEL

FENOFIBRIC ACID DELAYED-RELEASE CAPSULES

Rx Only

45 mg

NDC 68180-128-01

100 Tablets

FENOFIBRIC ACID DELAYED-RELEASE CAPSULES

Rx Only

135 mg

NDC 68180-129-01

100 Tablets